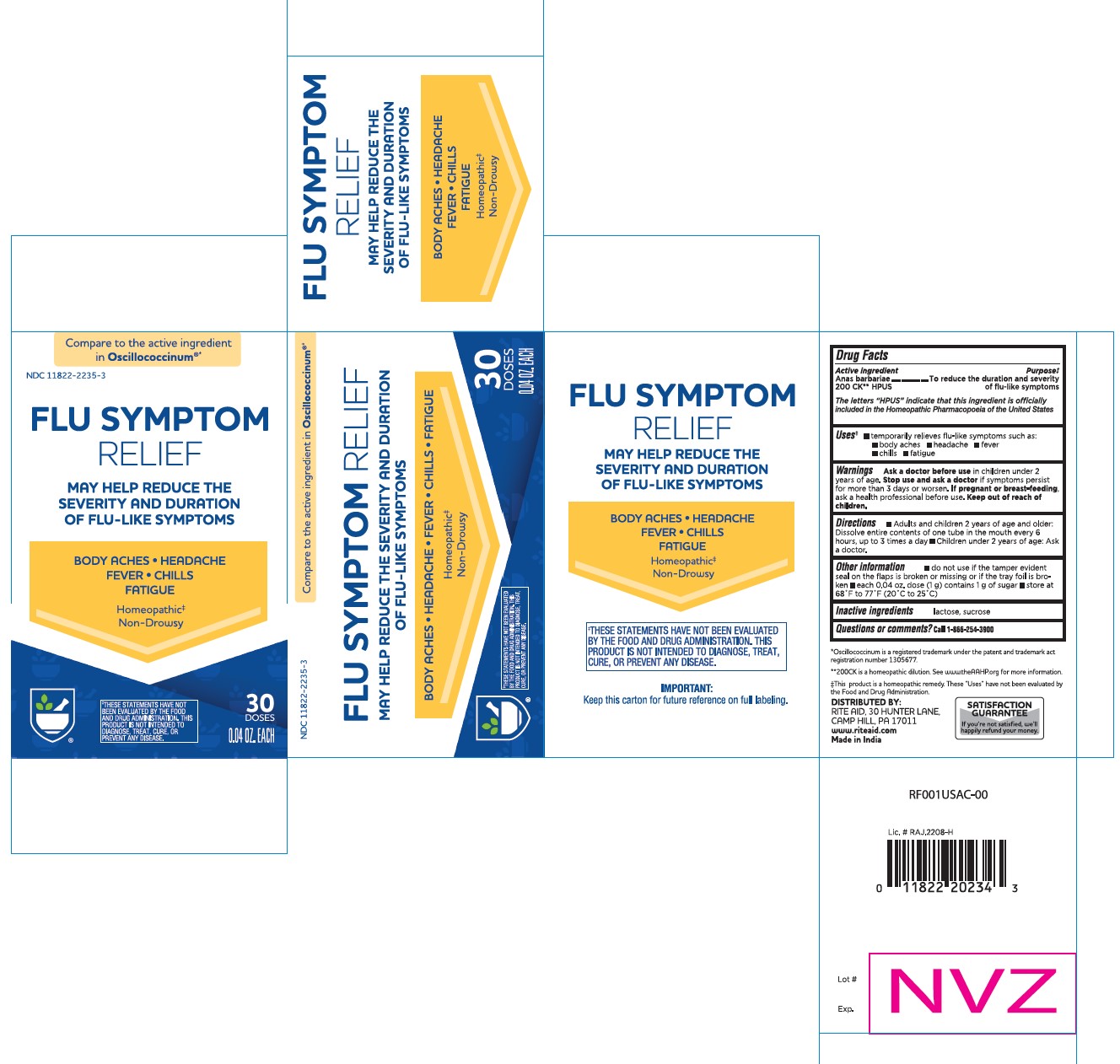 DRUG LABEL: CAIRINA MOSCHATA HEART/LIVER AUTOLYSATE
NDC: 11822-2235 | Form: PELLET
Manufacturer: Rite Aid Hdgrts Corp
Category: homeopathic | Type: HUMAN OTC DRUG LABEL
Date: 20241227

ACTIVE INGREDIENTS: CAIRINA MOSCHATA HEART/LIVER AUTOLYSATE 200 [hp_C]/1 1
INACTIVE INGREDIENTS: LACTOSE, UNSPECIFIED FORM; SUCROSE

Flu Symptom Relief

Active Ingredient Purpose

Anas barbariae 200 CK HPUS ............. To reduce the duration and severity of flu-like symptoms

The letters "HPUS" indicate that this ingredient is officially included in the Homeopathic Pharmacopoeia of the United States

USES

INDICATIONS AND USAGE

- Temporarily relieves ﬂu-like symptoms such as:
  - Body aches
  - Headache
  - Fever
  - Chills
  - Fatigue

WARNINGS

Warnings
Ask a doctor before use in children under 2 years of age.

Stop use and ask a doctor if symptoms persist for more than 3 days or worsen.

If pregnant or breast-feeding, ask a health professional before use.

Keep out of reach of children.

Directions

Adults and children 2 years of age and older:

- Dissolve entire contents of one tube in the mouth every 6 hours, up to 3 times a day
- Children under 2 years of age: Ask a doctor.

Other information

- do not use if the tamper evident seal on the flaps is broken or missing or if the tray foil is broken.
- each 0.04 oz. dose (1g) contains 1 g of sugar
- store at 68˚F to 77˚F (20˚C to 25˚C)

Questions or comments?
Call 1-866-254-3900.

Distributed by:

RITE AID, 30 HUNTER LANE,
CAMP HILL, PA 17011
www.riteaid.com
Made in India

Inactive ingredients

lactose, sucrose

- Compared to active ingredient in Oscillococcinum
- Oscillococcinum is a registered trademark under the patent and trademark act registration number 1305677.
- 200CK is a homeopathic dilution. See www.theAAHP.org for more information.
- This product is a homeopathic remedy. These “Uses” have not been evaluated by the Food and Drug Administration.